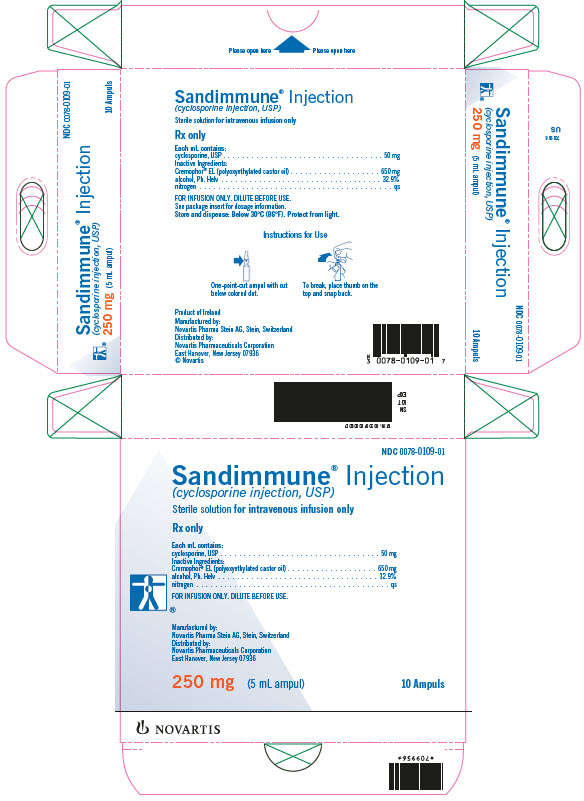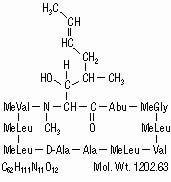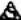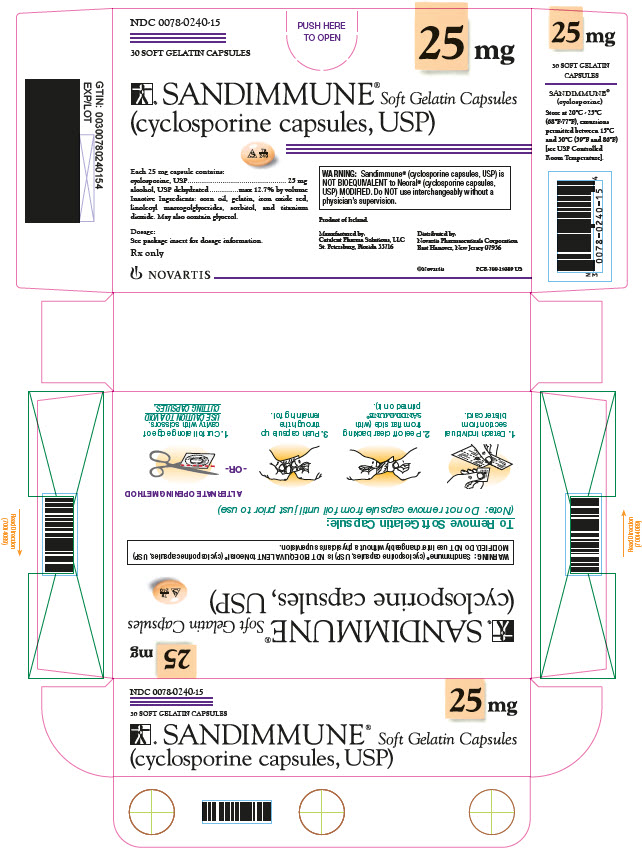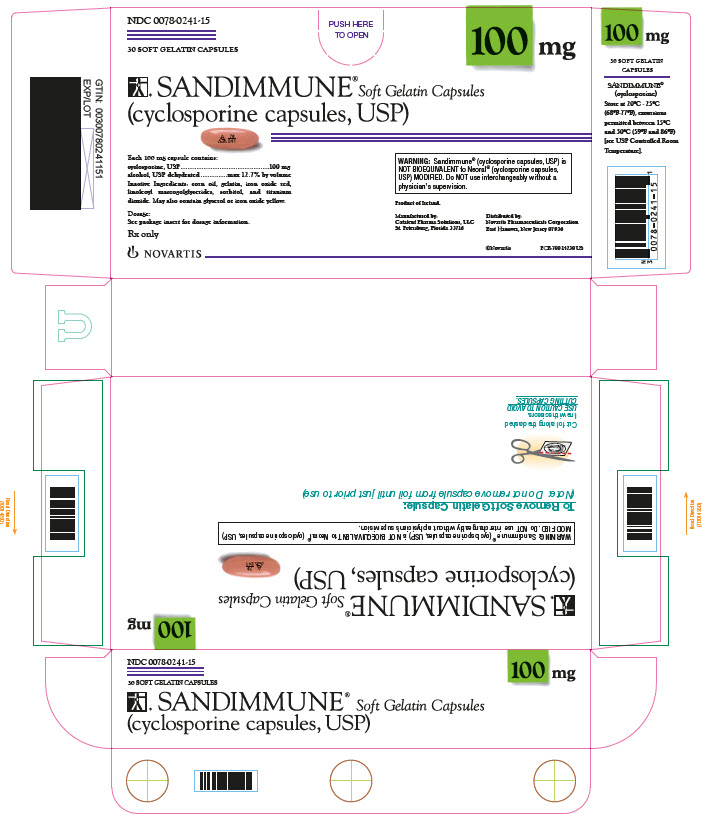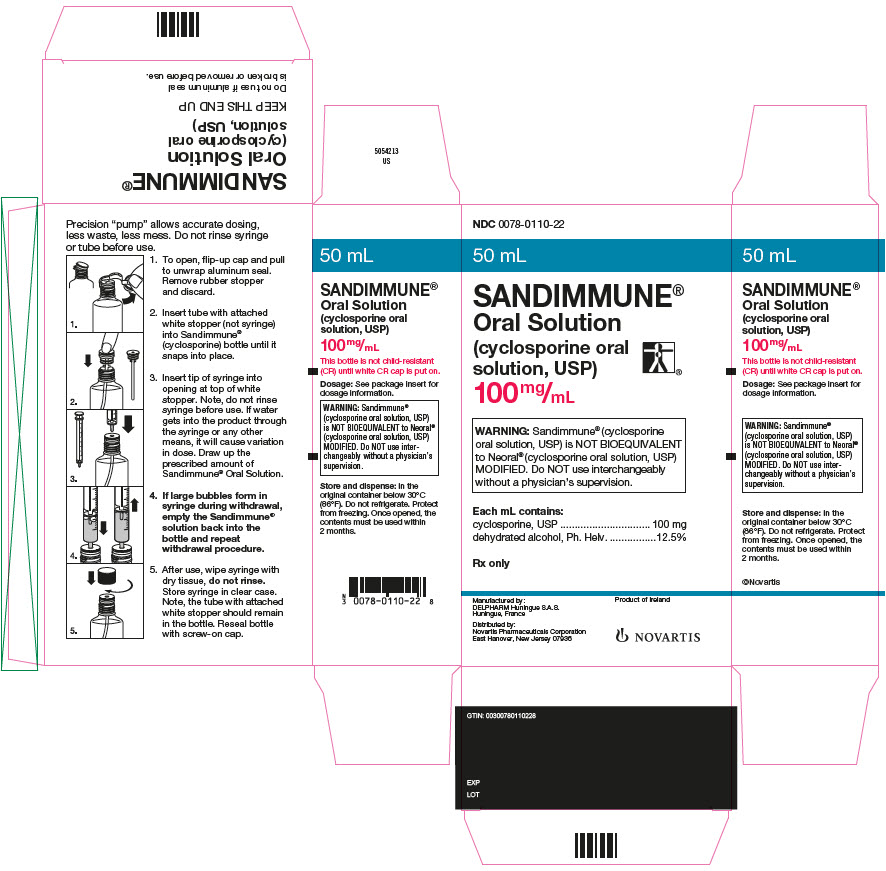 DRUG LABEL: Sandimmune
NDC: 0078-0240 | Form: CAPSULE, LIQUID FILLED
Manufacturer: Novartis Pharmaceuticals Corporation
Category: prescription | Type: HUMAN PRESCRIPTION DRUG LABEL
Date: 20251222

ACTIVE INGREDIENTS: CYCLOSPORINE 25 mg/1 1
INACTIVE INGREDIENTS: ALCOHOL; GELATIN; GLYCERIN; OLIVE OIL; FERRIC OXIDE RED; SORBITOL; TITANIUM DIOXIDE; CORN OIL; CASTOR OIL

Sandimmune® Soft Gelatin Capsules
(cyclosporine capsules, USP)
Sandimmune® Oral Solution
(cyclosporine oral solution, USP)
Sandimmune® Injection
(cyclosporine injection, USP)
FOR INFUSION ONLY
Rx only
Prescribing Information

WARNING

Only physicians experienced in immunosuppressive therapy and management of organ transplant patients should prescribe Sandimmune (cyclosporine). Patients receiving the drug should be managed in facilities equipped and staffed with adequate laboratory and supportive medical resources. The physician responsible for maintenance therapy should have complete information requisite for the follow-up of the patient.

Sandimmune (cyclosporine) should be administered with adrenal corticosteroids but not with other immunosuppressive agents. Increased susceptibility to infection and the possible development of lymphoma may result from immunosuppression.

Sandimmune Soft Gelatin Capsules (cyclosporine capsules, USP) and Sandimmune Oral Solution (cyclosporine oral solution, USP) have decreased bioavailability in comparison to Neoral Soft Gelatin Capsules (cyclosporine capsules, USP) MODIFIED and Neoral Oral Solution (cyclosporine oral solution, USP) MODIFIED.

Sandimmune and Neoral are not bioequivalent and cannot be used interchangeably without physician supervision.

The absorption of cyclosporine during chronic administration of Sandimmune Soft Gelatin Capsules and Oral Solution was found to be erratic. It is recommended that patients taking the soft gelatin capsules or oral solution over a period of time be monitored at repeated intervals for cyclosporine blood concentrations and subsequent dose adjustments be made in order to avoid toxicity due to high concentrations and possible organ rejection due to low absorption of cyclosporine. This is of special importance in liver transplants. Numerous assays are being developed to measure blood concentrations of cyclosporine. Comparison of concentrations in published literature to patient concentrations using current assays must be done with detailed knowledge of the assay methods employed (see DOSAGE AND ADMINISTRATION, Blood Concentration Monitoring).

DESCRIPTION

Cyclosporine, the active principle in Sandimmune (cyclosporine) is a cyclic polypeptide immunosuppressant agent consisting of 11 amino acids. It is produced as a metabolite by the fungus species Beauveria nivea.

Chemically, cyclosporine is designated as [R-[R*,R*-(E)]]-cyclic(L-alanyl-D-alanyl-N-methyl-L-leucyl-N-methyl-L-leucyl-N-methyl-L-valyl-3-hydroxy-N,4-dimethyl-L-2-amino-6-octenoyl-L-α-amino-butyryl-N-methylglycyl-N-methyl-L-leucyl-L-valyl-N-methyl-L-leucyl).

Sandimmune® Soft Gelatin Capsules (cyclosporine capsules, USP) are available in 25 mg and 100 mg strengths.

Each 25 mg capsule contains:

cyclosporine, USP…………………………………………………………………………………………25 mg

alcohol, USP dehydrated………………………………………………………………max 12.7% by volume

Each 100 mg capsule contains:

cyclosporine, USP……………………………………………………………………………………….100 mg

alcohol, USP dehydrated………………………………………………………………max 12.7% by volume

Inactive ingredients: corn oil, gelatin, iron oxide red, linoleoyl macrogolglycerides, sorbitol, and titanium dioxide. May also contain glycerol. 100 mg capsules may contain iron oxide yellow.

Sandimmune® Oral Solution (cyclosporine oral solution, USP) is available in 50 mL bottles.

Each mL contains:

cyclosporine, USP……………………………………………………………………………………….100 mg

alcohol, Ph. Helv. ……………………………………………………………………………12.5% by volume

dissolved in an olive oil, Ph. Helv./Labrafil M 1944 CS (polyoxyethylated oleic glycerides) vehicle which must be further diluted with milk, chocolate milk, or orange juice before oral administration.

Sandimmune® Injection (cyclosporine injection, USP) is available in a 5 mL sterile ampul for intravenous (IV) administration.

Each mL contains:

cyclosporine, USP…………………………………………………………………………………………50 mg

*Cremophor® EL (polyoxyethylated castor oil)………………………………………………………..650 mg

alcohol, Ph. Helv. ……………………………………………………………………………32.9% by volume

nitrogen………………………………………………………………………………………………………….qs

which must be diluted further with 0.9% Sodium Chloride Injection or 5% Dextrose Injection using appropriate aseptic technique before use.

The chemical structure of cyclosporine (also known as cyclosporin A) is

CLINICAL PHARMACOLOGY

Cyclosporine is a potent immunosuppressive agent, which in animals prolongs survival of allogeneic transplants involving skin, heart, kidney, pancreas, bone marrow, small intestine, and lung. Cyclosporine has been demonstrated to suppress some humoral immunity and to a greater extent, cell-mediated reactions, such as allograft rejection, delayed hypersensitivity, experimental allergic encephalomyelitis, Freund’s adjuvant arthritis, and graft vs. host disease in many animal species for a variety of organs.

Successful kidney, liver, and heart allogeneic transplants have been performed in man using cyclosporine.

The exact mechanism of action of cyclosporine is not known. Experimental evidence suggests that the effectiveness of cyclosporine is due to specific and reversible inhibition of immunocompetent lymphocytes in the G0- or G1-phase of the cell cycle. T-lymphocytes are preferentially inhibited. The T-helper cell is the main target, although the T-suppressor cell may also be suppressed. Cyclosporine also inhibits lymphokine production and release, including interleukin-2 or T-cell growth factor (TCGF).

No functional effects on phagocytic (changes in enzyme secretions not altered, chemotactic migration of granulocytes, macrophage migration, carbon clearance in vivo) or tumor cells (growth rate, metastasis) can be detected in animals. Cyclosporine does not cause bone marrow suppression in animal models or man.

The absorption of cyclosporine from the gastrointestinal tract is incomplete and variable. Peak concentrations (Cmax) in blood and plasma are achieved at about 3.5 hours. Cmax and area under the plasma or blood concentration/time curve (AUC) increase with the administered dose; for blood, the relationship is curvilinear (parabolic) between 0 and 1400 mg. As determined by a specific assay, Cmax is approximately 1.0 ng/mL/mg of dose for plasma and 2.7 to 1.4 ng/mL/mg of dose for blood (for low to high doses). Compared to an intravenous infusion, the absolute bioavailability of the oral solution is approximately 30% based upon the results in 2 patients. The bioavailability of Sandimmune Soft Gelatin Capsules (cyclosporine capsules, USP) is equivalent to Sandimmune Oral Solution, (cyclosporine oral solution, USP).

Cyclosporine is distributed largely outside the blood volume. In blood, the distribution is concentration dependent. Approximately 33% to 47% is in plasma, 4% to 9% in lymphocytes, 5% to 12% in granulocytes, and 41% to 58% in erythrocytes. At high concentrations, the uptake by leukocytes and erythrocytes becomes saturated. In plasma, approximately 90% is bound to proteins, primarily lipoproteins.

The disposition of cyclosporine from blood is biphasic with a terminal half-life of approximately 19 hours (range, 10 to 27 hours). Elimination is primarily biliary with only 6% of the dose excreted in the urine.

Cyclosporine is extensively metabolized but there is no major metabolic pathway. Only 0.1% of the dose is excreted in the urine as unchanged drug. Of 15 metabolites characterized in human urine, 9 have been assigned structures. The major pathways consist of hydroxylation of the Cγ-carbon of 2 of the leucine residues, Cη-carbon hydroxylation, and cyclic ether formation (with oxidation of the double bond) in the side chain of the amino acid 3-hydroxyl-N,4-dimethyl-L-2-amino-6-octenoic acid and N-demethylation of N-methyl leucine residues. Hydrolysis of the cyclic peptide chain or conjugation of the aforementioned metabolites do not appear to be important biotransformation pathways.

Specific Populations

Renal Impairment

In a study performed in 4 subjects with end-stage renal disease (creatinine clearance < 5 mL/min), an intravenous infusion of 3.5 mg/kg of cyclosporine over 4 hours administered at the end of a hemodialysis session resulted in a mean volume of distribution (Vdss) of 3.49 L/kg and systemic clearance (CL) of 0.369 L/hr/kg. This systemic CL (0.369 L/hr/kg) was approximately two thirds of the mean systemic CL (0.56 L/hr/kg) of cyclosporine in historical control subjects with normal renal function. In 5 liver transplant patients, the mean clearance of cyclosporine on and off hemodialysis was 463 mL/min and 398 mL/min, respectively. Less than 1% of the dose of cyclosporine was recovered in the dialysate.

Hepatic Impairment

Cyclosporine is extensively metabolized by the liver. Since severe hepatic impairment may result in significantly increased cyclosporine exposures, the dosage of cyclosporine may need to be reduced in these patients.

INDICATIONS AND USAGE

Sandimmune (cyclosporine) is indicated for the prophylaxis of organ rejection in kidney, liver, and heart allogeneic transplants. It is always to be used with adrenal corticosteroids. The drug may also be used in the treatment of chronic rejection in patients previously treated with other immunosuppressive agents.

Because of the risk of anaphylaxis, Sandimmune Injection (cyclosporine injection, USP) should be reserved for patients who are unable to take the soft gelatin capsules or oral solution.

CONTRAINDICATIONS

Sandimmune Injection (cyclosporine injection, USP) is contraindicated in patients with a hypersensitivity to Sandimmune (cyclosporine) and/or Cremophor® EL (polyoxyethylated castor oil).

WARNINGS

Kidney, Liver, and Heart Transplant

Sandimmune (cyclosporine), when used in high doses, can cause hepatotoxicity and nephrotoxicity (see BOXED WARNING).

Nephrotoxicity

It is not unusual for serum creatinine and BUN levels to be elevated during Sandimmune (cyclosporine) therapy. These elevations in renal transplant patients do not necessarily indicate rejection, and each patient must be fully evaluated before dosage adjustment is initiated.

Nephrotoxicity has been noted in 25% of cases of renal transplantation, 38% of cases of cardiac transplantation, and 37% of cases of liver transplantation. Mild nephrotoxicity was generally noted 2 to 3 months after transplant and consisted of an arrest in the fall of the preoperative elevations of BUN and creatinine at a range of 35 to 45 mg/dl and 2.0 to 2.5 mg/dl, respectively. These elevations were often responsive to dosage reduction.

More overt nephrotoxicity was seen early after transplantation and was characterized by a rapidly rising BUN and creatinine. Since these events are similar to rejection episodes, care must be taken to differentiate between them. This form of nephrotoxicity is usually responsive to Sandimmune (cyclosporine) dosage reduction.

Although specific diagnostic criteria which reliably differentiate renal graft rejection from drug toxicity have not been found, a number of parameters have been significantly associated to one or the other. It should be noted however, that up to 20% of patients may have simultaneous nephrotoxicity and rejection.

 | Nephrotoxicity vs. Rejection
Parameter | Nephrotoxicity | Rejection
History | Donor > 50 years old or hypotensive | Antidonor immune response
 | Prolonged kidney preservation | Retransplant patient
 | Prolonged anastomosis time
 | Concomitant nephrotoxic drugs
Clinical | Often > 6 weeks postopb | Often < 4 weeks postopb
 | Prolonged initial nonfunction (acute tubular necrosis) | Fever > 37.5°C
 |  | Weight gain > 0.5 kg
 |  | Graft swelling and tenderness
 |  | Decrease in daily urine volume > 500 mL (or 50%)
Laboratory | CyA serum trough level > 200 ng/mL | CyA serum trough level < 150 ng/mL
 | Gradual rise in Cr (< 0.15 mg/dL/day)a | Rapid rise in Cr (> 0.3 mg/dL/day)a
 | Cr plateau < 25% above baseline | Cr > 25% above baseline
 | BUN/Cr ≥ 20 | BUN/Cr < 20
Biopsy | Arteriolopathy (medial hypertrophya, hyalinosis, nodular deposits, intimal thickening, endothelial vacuolization, progressive scarring) | Endovasculitisc (proliferationa, intimal arteritisb, necrosis, sclerosis)
 | Tubular atrophy, isometric vacuolization, isolated calcifications | Tubulitis with RBCb and WBCb casts, some irregular vacuolization
 | Minimal edema | Interstitial edemac and hemorrhageb
 | Mild focal infiltratesc | Diffuse moderate to severe mononuclear infiltratesd
 | Diffuse interstitial fibrosis, often striped form | Glomerulitis (mononuclear cells)c
Aspiration Cytology | CyA deposits in tubular and endothelial cells | Inflammatory infiltrate with mononuclear phagocytes, macrophages, lymphoblastoid cells, and activated T-cells
 | Fine isometric vacuolization of tubular cells | These strongly express HLA-DR antigens
Urine Cytology | Tubular cells with vacuolization and granularization | Degenerative tubular cells, plasma cells, and lymphocyturia > 20% of sediment
Manometry | Intracapsular pressure < 40 mm Hgb | Intracapsular pressure > 40 mm Hgb
Ultrasonography | Unchanged graft cross-sectional area | Increase in graft cross-sectional area
 |  | AP diameter ≥ Transverse diameter
Magnetic Resonance Imagery | Normal appearance | Loss of distinct corticomedullary junction, swelling, image intensity of parachyma approaching that of psoas, loss of hilar fat
Radionuclide Scan | Normal or generally decreased perfusion | Patchy arterial flow
 | Decrease in tubular function | Decrease in perfusion > decrease in tubular function
 | (^131 I-hippuran) > decrease in perfusion (99m Tc DTPA) | Increased uptake of Indium 111 labeled platelets or Tc-99m in colloid
Therapy | Responds to decreased Sandimmune (cyclosporine) | Responds to increased steroids or antilymphocyte globulin
ap < 0.05, bp < 0.01, cp < 0.001, dp < 0.0001.

A form of chronic progressive cyclosporine-associated nephrotoxicity is characterized by serial deterioration in renal function and morphologic changes in the kidneys. From 5% to 15% of transplant recipients will fail to show a reduction in a rising serum creatinine despite a decrease or discontinuation of cyclosporine therapy. Renal biopsies from these patients will demonstrate an interstitial fibrosis with tubular atrophy. In addition, toxic tubulopathy, peritubular capillary congestion, arteriolopathy, and a striped form of interstitial fibrosis with tubular atrophy may be present. Though none of these morphologic changes is entirely specific, a histologic diagnosis of chronic progressive cyclosporine-associated nephrotoxicity requires evidence of these.

When considering the development of chronic nephrotoxicity, it is noteworthy that several authors have reported an association between the appearance of interstitial fibrosis and higher cumulative doses or persistently high circulating trough concentrations of cyclosporine. This is particularly true during the first 6 posttransplant months when the dosage tends to be highest and when, in kidney recipients, the organ appears to be most vulnerable to the toxic effects of cyclosporine. Among other contributing factors to the development of interstitial fibrosis in these patients must be included, prolonged perfusion time, warm ischemia time, as well as episodes of acute toxicity, and acute and chronic rejection. The reversibility of interstitial fibrosis and its correlation to renal function have not yet been determined.

Impaired renal function at any time requires close monitoring, and frequent dosage adjustment may be indicated. In patients with persistent high elevations of BUN and creatinine who are unresponsive to dosage adjustments, consideration should be given to switching to other immunosuppressive therapy. In the event of severe and unremitting rejection, it is preferable to allow the kidney transplant to be rejected and removed rather than increase the Sandimmune (cyclosporine) dosage to a very high level in an attempt to reverse the rejection.

Due to the potential for additive or synergistic impairment of renal function, caution should be exercised when coadministering Sandimmune with other drugs that may impair renal function (see PRECAUTIONS, Drug Interactions).

Thrombotic Microangiopathy

Occasionally patients have developed a syndrome of thrombocytopenia and microangiopathic hemolytic anemia which may result in graft failure. The vasculopathy can occur in the absence of rejection and is accompanied by avid platelet consumption within the graft as demonstrated by Indium 111 labeled platelet studies. Neither the pathogenesis nor the management of this syndrome is clear. Though resolution has occurred after reduction or discontinuation of Sandimmune (cyclosporine) and 1) administration of streptokinase and heparin or 2) plasmapheresis, this appears to depend upon early detection with Indium 111 labeled platelet scans (see ADVERSE REACTIONS).

Hyperkalemia

Significant hyperkalemia (sometimes associated with hyperchloremic metabolic acidosis) and hyperuricemia have been seen occasionally in individual patients.

Hepatotoxicity

Cases of hepatotoxicity and liver injury, including cholestasis, jaundice, hepatitis, and liver failure have been reported in patients treated with cyclosporine. Most reports included patients with significant co-morbidities, underlying conditions and other confounding factors, including infectious complications and comedications with hepatotoxic potential. In some cases, mainly in transplant patients, fatal outcomes have been reported (see ADVERSE REACTIONS, Postmarketing Experience).

Hepatotoxicity, usually manifested by elevations in hepatic enzymes and bilirubin, was reported in patients treated with cyclosporine in clinical trials: 4% in renal transplantation, 7% in cardiac transplantation, and 4% in liver transplantation. This was usually noted during the first month of therapy when high doses of Sandimmune (cyclosporine) were used. The chemistry elevations usually decreased with a reduction in dosage.

Malignancies

As in patients receiving other immunosuppressants, those patients receiving Sandimmune (cyclosporine) are at increased risk for development of lymphomas and other malignancies, particularly those of the skin. The increased risk appears related to the intensity and duration of immunosuppression rather than to the use of specific agents. Because of the danger of oversuppression of the immune system, which can also increase susceptibility to infection, Sandimmune (cyclosporine) should not be administered with other immunosuppressive agents except adrenal corticosteroids. The efficacy and safety of cyclosporine in combination with other immunosuppressive agents have not been determined. Some malignancies may be fatal. Transplant patients receiving cyclosporine are at increased risk for serious infection with fatal outcome.

Serious Infections

Patients receiving immunosuppressants, including Sandimmune, are at increased risk of developing bacterial, viral, fungal, and protozoal infections, including opportunistic infections. These infections may lead to serious, including fatal, outcomes (see BOXED WARNING and ADVERSE REACTIONS).

Polyoma Virus Infections

Patients receiving immunosuppressants, including Sandimmune, are at increased risk for opportunistic infections, including polyoma virus infections. Polyoma virus infections in transplant patients may have serious, and sometimes, fatal outcomes. These include cases of JC virus-associated progressive multifocal leukoencephalopathy (PML), and polyoma virus-associated nephropathy (PVAN), especially due to BK virus infection, which have been observed in patients receiving cyclosporine.

PVAN is associated with serious outcomes, including deteriorating renal function and renal graft loss, (see ADVERSE REACTIONS, Postmarketing Experience). Patient monitoring may help detect patients at risk for PVAN.

Cases of PML have been reported in patients treated with Sandimmune. PML, which is sometimes fatal, commonly presents with hemiparesis, apathy, confusion, cognitive deficiencies, and ataxia. Risk factors for PML include treatment with immunosuppressant therapies and impairment of immune function. In immunosuppressed patients, physicians should consider PML in the differential diagnosis in patients reporting neurological symptoms and consultation with a neurologist should be considered as clinically indicated.

Consideration should be given to reducing the total immunosuppression in transplant patients who develop PML or PVAN. However, reduced immunosuppression may place the graft at risk.

Neurotoxicity

There have been reports of convulsions in adult and pediatric patients receiving cyclosporine, particularly in combination with high-dose methylprednisolone.

Encephalopathy, including Posterior Reversible Encephalopathy Syndrome (PRES), has been described both in postmarketing reports and in the literature. Manifestations include impaired consciousness, convulsions, visual disturbances (including blindness), loss of motor function, movement disorders, and psychiatric disturbances. In many cases, changes in the white matter have been detected using imaging techniques and pathologic specimens. Predisposing factors such as hypertension, hypomagnesemia, hypocholesterolemia, high-dose corticosteroids, high cyclosporine blood concentrations, and graft-versus-host disease have been noted in many but not all of the reported cases. The changes in most cases have been reversible upon discontinuation of cyclosporine, and in some cases, improvement was noted after reduction of dose. It appears that patients receiving liver transplant are more susceptible to encephalopathy than those receiving kidney transplant. Another rare manifestation of cyclosporine-induced neurotoxicity is optic disc edema, including papilloedema, with possible visual impairment, secondary to benign intracranial hypertension.

Specific Excipients

Anaphylactic Reactions

Rarely (approximately 1 in 1000), patients receiving Sandimmune Injection (cyclosporine injection, USP) have experienced anaphylactic reactions. Although the exact cause of these reactions is unknown, it is believed to be due to the Cremophor EL (polyoxyethylated castor oil) used as the vehicle for the intravenous (IV) formulation. These reactions can consist of flushing of the face and upper thorax, and noncardiogenic pulmonary edema, with acute respiratory distress, dyspnea, wheezing, blood pressure changes, and tachycardia. One patient died after respiratory arrest and aspiration pneumonia. In some cases, the reaction subsided after the infusion was stopped.

Patients receiving Sandimmune Injection (cyclosporine injection, USP) should be under continuous observation for at least the first 30 minutes following the start of the infusion and at frequent intervals thereafter. If anaphylaxis occurs, the infusion should be stopped. An aqueous solution of epinephrine 1:1000 should be available at the bedside as well as a source of oxygen.

Anaphylactic reactions have not been reported with the soft gelatin capsules or oral solution which lack Cremophor EL (polyoxyethylated castor oil). In fact, patients experiencing anaphylactic reactions have been treated subsequently with the soft gelatin capsules or oral solution without incident.

Alcohol (ethanol)

The alcohol content (see DESCRIPTION) of Sandimmune should be taken into account when given to patients in whom alcohol intake should be avoided or minimized, e.g., pregnant or breastfeeding women, in patients presenting with liver disease or epilepsy, in alcoholic patients, or pediatric patients. For an adult weighing 70 kg, the maximum daily oral dose would deliver about 1 gram of alcohol (see DESCRIPTION for alcohol content of each formulation).

Care should be taken in using Sandimmune (cyclosporine) with nephrotoxic drugs (see PRECAUTIONS).

Conversion from Neoral to Sandimmune

Because Sandimmune (cyclosporine) is not bioequivalent to Neoral, conversion from Neoral to Sandimmune (cyclosporine) using a 1:1 ratio (mg/kg/day) may result in a lower cyclosporine blood concentration. Conversion from Neoral to Sandimmune (cyclosporine) should be made with increased blood concentration monitoring to avoid the potential of underdosing.

PRECAUTIONS

General

Patients with malabsorption may have difficulty in achieving therapeutic concentrations with Sandimmune Soft Gelatin Capsules or Oral Solution.

Hypertension

Hypertension is a common side effect of Sandimmune (cyclosporine) therapy (see ADVERSE REACTIONS). Mild or moderate hypertension is more frequently encountered than severe hypertension and the incidence decreases over time. Antihypertensive therapy may be required. Control of blood pressure can be accomplished with any of the common antihypertensive agents. However, since cyclosporine may cause hyperkalemia, potassium-sparing diuretics should not be used. While calcium antagonists can be effective agents in treating cyclosporine-associated hypertension, care should be taken since interference with cyclosporine metabolism may require a dosage adjustment (see Drug Interactions).

Vaccination

During treatment with Sandimmune (cyclosporine), vaccination may be less effective and the use of live attenuated vaccines should be avoided.

Information for Patients

Patients should be advised that any change of cyclosporine formulation should be made cautiously and only under physician supervision because it may result in the need for a change in dosage.

Patients should be informed of the necessity of repeated laboratory tests while they are receiving the drug. They should be given careful dosage instructions, advised of the potential risks during pregnancy, and informed of the increased risk of neoplasia.

Patients using cyclosporine oral solution with its accompanying syringe for dosage measurement should be cautioned not to rinse the syringe either before or after use. Introduction of water into the product by any means will cause variation in dose.

Cyclosporine may impact the ability to drive and use machines. Patients should be advised to exercise care when driving or using machines if they experience neurological disturbances including confusion, somnolence, or dizziness and discuss with their healthcare provider (see WARNINGS and ADVERSE REACTIONS).

Laboratory Tests

Renal and liver functions should be assessed repeatedly by measurement of BUN, serum creatinine, serum bilirubin, and liver enzymes.

Drug Interactions

A. Effect of Drugs and Other Agents on Cyclosporine Pharmacokinetics and/or Safety

All of the individual drugs cited below are well substantiated to interact with cyclosporine. In addition, concomitant use of nonsteroidal anti-inflammatory drugs (NSAIDs) with cyclosporine, particularly in the setting of dehydration, may potentiate renal dysfunction. Caution should be exercised when using other drugs which are known to impair renal function (see WARNINGS, Nephrotoxicity).

Drugs That May Potentiate Renal Dysfunction

Antibiotics | Antineoplastic | Antifungals | Anti-Inflammatory Drugs | Gastrointestinal Agents | Immunosuppressives | Other Drugs
ciprofloxacin | melphalan | amphotericin B | azapropazon | cimetidine | tacrolimus | fibric acid derivatives (e.g., bezafibrate, fenofibrate)
gentamicin |  | ketoconazole | colchicine | ranitidine |  | methotrexate
tobramycin |  |  | diclofenac
trimethoprim with sulfamethoxazole |  |  | naproxen
vancomycin |  |  | sulindac

During the concomitant use of a drug that may exhibit additive or synergistic renal impairment potential with cyclosporine, close monitoring of renal function (in particular serum creatinine) should be performed. If a significant impairment of renal function occurs, reduction in the dosage of cyclosporine and/or coadministered drug or an alternative treatment should be considered.

Cyclosporine is extensively metabolized by CYP 3A isoenzymes, in particular CYP3A4, and is a substrate of the multidrug efflux transporter P-glycoprotein. Various agents are known to either increase or decrease plasma or whole blood concentrations of cyclosporine usually by inhibition or induction of CYP3A4 or P-glycoprotein transporter or both. Compounds that decrease cyclosporine absorption, such as orlistat, should be avoided. Appropriate Sandimmune (cyclosporine) dosage adjustment to achieve the desired cyclosporine concentrations is essential when drugs that significantly alter cyclosporine concentrations are used concomitantly (see DOSAGE AND ADMINISTRATION, Blood Concentration Monitoring).

1. Drugs That Increase Cyclosporine Concentrations

Calcium Channel Blockers | Antifungals | Antibiotics | Glucocorticoids | Other Drugs
diltiazem | fluconazole | azithromycin | methylprednisolone | allopurinol
nicardipine | itraconazole | clarithromycin |  | amiodarone
verapamil | ketoconazole | erythromycin |  | bromocriptine
 | voriconazole | quinupristin/ dalfopristin |  | colchicine
 |  |  |  | danazol
 |  |  |  | imatinib
 |  |  |  | metoclopramide
 |  |  |  | nefazodone
 |  |  |  | oral contraceptives

HIV Protease inhibitors

The HIV protease inhibitors (e.g., indinavir, nelfinavir, ritonavir, and saquinavir) are known to inhibit cytochrome P-450 3A and thus could potentially increase the concentrations of cyclosporine, however, no formal studies of the interaction are available. Care should be exercised when these drugs are administered concomitantly.

Grapefruit Juice

Grapefruit and grapefruit juice affect metabolism, increasing blood concentrations of cyclosporine, thus should be avoided.

2. Drugs/Dietary Supplements That Decrease Cyclosporine Concentrations

Antibiotics | Anticonvulsants | Other Drugs / Dietary Supplements
nafcillin | carbamazepine | bosentan | St. John’s Wort
rifampin | oxcarbazepine | octreotide
 | phenobarbital | orlistat
 | phenytoin | sulfinpyrazone
 |  | terbinafine
 |  | ticlopidine

Bosentan

Coadministration of bosentan (250 to 1000 mg every 12 hours based on tolerability) and cyclosporine (300 mg every 12 hours for 2 days then dosing to achieve a Cmin of 200 to 250 ng/mL) for 7 days in healthy subjects resulted in decreases in the cyclosporine mean dose-normalized AUC, Cmax, and trough concentration of approximately 50%, 30% and 60%, respectively, compared to when cyclosporine was given alone (see also Effect of Cyclosporine on the Pharmacokinetics and/or Safety of Other Drugs or Agents). Coadministration of cyclosporine with bosentan should be avoided.

Boceprevir

Coadministration of boceprevir (800 mg three times daily for 7 days) and cyclosporine (100 mg single dose) in healthy subjects resulted in increases in the mean AUC and Cmax of cyclosporine approximately 2.7-fold and 2-fold, respectively, compared to when cyclosporine was given alone.

Telaprevir

Coadministration of telaprevir (750 mg every 8 hours for 11 days) with cyclosporine (10 mg on Day 8) in healthy subjects resulted in increases in the mean dose-normalized AUC and Cmax of cyclosporine approximately 4.5-fold and 1.3-fold, respectively, compared to when cyclosporine (100 mg single dose) was given alone.

St. John’s Wort

There have been reports of a serious drug interaction between cyclosporine and the herbal dietary supplement, St. John’s Wort. This interaction has been reported to produce a marked reduction in the blood concentrations of cyclosporine, resulting in subtherapeutic levels, rejection of transplanted organs, and graft loss.

Rifabutin

Rifabutin is known to increase the metabolism of other drugs metabolized by the cytochrome P-450 system. The interaction between rifabutin and cyclosporine has not been studied. Care should be exercised when these two drugs are administered concomitantly.

B. Effect of Cyclosporine on the Pharmacokinetics and/or Safety of Other Drugs or Agents

Cyclosporine is an inhibitor of CYP3A4 and of multiple drug efflux transporters (e.g., P-glycoprotein) and may increase plasma concentrations of comedications that are substrates of CYP3A4, P-glycoprotein, or organic anion transporter proteins.

Cyclosporine may reduce the clearance of digoxin, colchicine, prednisolone, HMG-CoA reductase inhibitors (statins) and aliskiren, bosentan, dabigatran, repaglinide, NSAIDs, sirolimus, etoposide, and other drugs.

See the full prescribing information of the other drug for further information and specific recommendations. The decision on coadministration of cyclosporine with other drugs or agents should be made by the healthcare provider following the careful assessment of benefits and risks.

Digoxin

Severe digitalis toxicity has been seen within days of starting cyclosporine in several patients taking digoxin. If digoxin is used concurrently with cyclosporine, serum digoxin concentrations should be monitored.

Colchicine

There are reports on the potential of cyclosporine to enhance the toxic effects of colchicine, such as myopathy and neuropathy, especially in patients with renal dysfunction. Concomitant administration of cyclosporine and colchicine results in significant increases in colchicine plasma concentrations. If colchicine is used concurrently with cyclosporine, a reduction in the dosage of colchicine is recommended.

HMG Co-A Reductase Inhibitors (Statins)

Literature and postmarketing cases of myotoxicity, including muscle pain and weakness, myositis, and rhabdomyolysis, have been reported with concomitant administration of cyclosporine with lovastatin, simvastatin, atorvastatin, pravastatin, and rarely, fluvastatin. When concurrently administered with cyclosporine, the dosage of these statins should be reduced according to label recommendations. Statin therapy needs to be temporarily withheld or discontinued in patients with signs and symptoms of myopathy or those with risk factors predisposing to severe renal injury, including renal failure, secondary to rhabdomyolysis.

Repaglinide

Cyclosporine may increase the plasma concentrations of repaglinide and thereby increase the risk of hypoglycemia. In 12 healthy male subjects who received two doses of 100 mg cyclosporine capsule orally 12 hours apart with a single dose of 0.25 mg repaglinide tablet (one half of a 0.5 mg tablet) orally 13 hours after the cyclosporine initial dose, the repaglinide mean Cmax and AUC were increased 1.8-fold (range, 0.6 to 3.7-fold) and 2.4-fold (range, 1.2 to 5.3-fold), respectively. Close monitoring of blood glucose level is advisable for a patient taking cyclosporine and repaglinide concomitantly.

Ambrisentan

Coadministration of ambrisentan (5 mg daily) and cyclosporine (100 to 150 mg twice daily initially, then dosing to achieve Cmin 150 to 200 ng/mL) for 8 days in healthy subjects resulted mean increases in ambrisentan AUC and Cmax of approximately 2-fold and 1.5-fold, respectively, compared to ambrisentan alone. When coadministering ambrisentan with cyclosporine, the ambrisentan dose should not be titrated to the recommended maximum daily dose.

Anthracycline Antibiotics

High doses of cyclosporine (e.g., at starting intravenous dose of 16 mg/kg/day) may increase the exposure to anthracycline antibiotics (e.g., doxorubicin, mitoxantrone, daunorubicin) in cancer patients.

Aliskiren

Cyclosporine alters the pharmacokinetics of aliskiren, a substrate of P-glycoprotein and CYP3A4. In 14 healthy subjects who received concomitantly single doses of cyclosporine (200 mg) and reduced dose aliskiren (75 mg), the mean Cmax of aliskiren was increased by approximately 2.5-fold (90% CI: 1.96 to 3.17) and the mean AUC by approximately 4.3-fold (90% CI: 3.52 to 5.21), compared to when these subjects received aliskiren alone. The concomitant administration of aliskiren with cyclosporine prolonged the median aliskiren elimination half-life (26 hours versus 43 to 45 hours) and the Tmax (0.5 hours versus 1.5 to 2.0 hours). The mean AUC and Cmax of cyclosporine were comparable to reported literature values. Coadministration of cyclosporine and aliskiren in these subjects also resulted in an increase in the number and/or intensity of adverse events, mainly headache, hot flush, nausea, vomiting, and somnolence. The coadministration of cyclosporine with aliskiren is not recommended.

Bosentan

In healthy subjects, coadministration of bosentan and cyclosporine resulted in time-dependent mean increases in dose-normalized bosentan trough concentrations (i.e., approximately 21-fold on Day 1 and 2-fold on Day 8 (steady state)) compared to when bosentan was given alone as a single dose on Day 1 (see also Effect of Drugs and Other Agents on Cyclosporine Pharmacokinetics and/or Safety). Coadministration of cyclosporine with bosentan should be avoided.

Dabigatran

The effect of cyclosporine on dabigatran concentrations had not been formally studied. Concomitant administration of dabigatran and cyclosporine may result in increased plasma dabigatran concentrations due to the P-gp inhibitory activity of cyclosporine. Coadministration of cyclosporine with dabigatran should be avoided.

Potassium Sparing Diuretics

Cyclosporine should not be used with potassium-sparing diuretics because hyperkalemia can occur. Caution is also required when cyclosporine is coadministered with potassium-sparing drugs (e.g., angiotensin-converting enzyme inhibitors, angiotensin II receptor antagonists), potassium-containing drugs as well as in patients on a potassium-rich diet. Control of potassium levels in these situations is advisable.

Nonsteroidal Anti-inflammatory Drug (NSAID) Interactions

Clinical status and serum creatinine should be closely monitored when cyclosporine is used with NSAIDs in rheumatoid arthritis patients (see WARNINGS).

Pharmacodynamic interactions have been reported to occur between cyclosporine and both naproxen and sulindac, in that concomitant use is associated with additive decreases in renal function, as determined by 99mTc-diethylenetriaminepenta acetic acid (DTPA) and (p-aminohippuric acid) PAH clearances. Although concomitant administration of diclofenac does not affect blood concentrations of cyclosporine, it has been associated with approximate doubling of diclofenac blood levels and occasional reports of reversible decreases in renal function. Consequently, the dose of diclofenac should be in the lower end of the therapeutic range.

Methotrexate Interaction

Preliminary data indicate that when methotrexate and cyclosporine were coadministered to rheumatoid arthritis patients (N = 20), methotrexate concentrations (AUCs) were increased approximately 30% and the concentrations (AUCs) of its metabolite, 7-hydroxy methotrexate, were decreased by approximately 80%. The clinical significance of this interaction is not known. Cyclosporine concentrations do not appear to have been altered (N = 6).

Sirolimus

Elevations in serum creatinine were observed in studies using sirolimus in combination with full-dose cyclosporine. This effect is often reversible with cyclosporine dose reduction. Simultaneous coadministration of cyclosporine significantly increases blood levels of sirolimus. To minimize increases in sirolimus blood concentrations, it is recommended that sirolimus be given 4 hours after cyclosporine administration.

Nifedipine

Frequent gingival hyperplasia when nifedipine is given concurrently with cyclosporine has been reported. The concomitant use of nifedipine should be avoided in patients in whom gingival hyperplasia develops as a side effect of cyclosporine.

Methylprednisolone

Convulsions when high dose methylprednisolone is given concomitantly with cyclosporine have been reported.

Other Immunosuppressive Drugs and Agents

Psoriasis patients receiving other immunosuppressive agents or radiation therapy (including PUVA and UVB) should not receive concurrent cyclosporine because of the possibility of excessive immunosuppression.

Interactions Resulting in Decrease of Other Drug Levels

Cyclosporine inhibits the enterohepatic circulation of mycophenolic acid (MPA). Concomitant administration of cyclosporine and mycophenolate mofetil or mycophenolate sodium in transplant patients may decrease the mean exposure of MPA by 20% to 50% when compared with other immunosuppressants, which could reduce efficacy of mycophenolate mofetil or mycophenolate sodium. Monitor patients for alterations in efficacy of mycophenolate mofetil or mycophenolate sodium, when they are coadministered with cyclosporine.

C. Effect of Cyclosporine on the Efficacy of Live Vaccines

During treatment with cyclosporine, vaccination may be less effective. The use of live vaccines should be avoided.

For additional information on Cyclosporine Drug Interactions please contact Novartis Medical Affairs Department at 1-888-NOW-NOVA (1-888-669-6682).

Carcinogenesis, Mutagenesis, and Impairment of Fertility

Cyclosporine gave no evidence of mutagenic or teratogenic effects in appropriate test systems. Only at dose levels toxic to dams, were adverse effects seen in reproduction studies in rats (see Pregnancy).

Carcinogenicity studies were carried out in male and female rats and mice. In the 78-week mouse study, at doses of 1, 4, and 16 mg/kg/day, evidence of a statistically significant trend was found for lymphocytic lymphomas in females, and the incidence of hepatocellular carcinomas in mid-dose (0.03 times the maximum recommended human dose (MRHD) based on body surface area (BSA) males significantly exceeded the control value. In the 24–month rat study, conducted at 0.5, 2, and 8 mg/kg/day, pancreatic islet cell adenomas significantly exceeded the control rate in the low-dose level (0.006 times the MRHD based on BSA). The hepatocellular carcinomas and pancreatic islet cell adenomas were not dose related.

Cyclosporine has not been found mutagenic/genotoxic in the Ames test, the V79-HGPRT Test, the micronucleus test in mice and Chinese hamsters, the chromosome-aberration tests in Chinese hamster bone marrow, the mouse dominant lethal assay, and the DNA-repair test in sperm from treated mice. A recent study analyzing sister chromatid exchange (SCE) induction by cyclosporine using human lymphocytes in vitro gave indication of a positive effect (i.e., induction of SCE), at high concentrations in this system.

In a fertility study in rats, increased perinatal mortality and impaired postnatal development of F1 pups were observed at 15 mg/kg/day (0.2 times the MRHD based on BSA). No adverse effects on fertility and reproduction were observed up to 5 mg/kg/day (0.06 times the MRHD based on BSA) in male and female rats.

An increased incidence of malignancy is a recognized complication of immunosuppression in recipients of organ transplants. The most common forms of neoplasms are non-Hodgkin’s lymphoma and carcinomas of the skin. The risk of malignancies in cyclosporine recipients is higher than in the normal, healthy population, but similar to that in patients receiving other immunosuppressive therapies. It has been reported that reduction or discontinuance of immunosuppression may cause the lesions to regress.

Pregnancy

Pregnancy Exposure Registry

There is a pregnancy exposure registry that monitors pregnancy outcomes in women exposed to cyclosporine, including Sandimmune, during pregnancy. Encourage women who are taking Sandimmune during pregnancy to enroll in the Transplant Pregnancy Registry International (TPRI) by calling 1-877-955-8677 or visiting https://www.transplantpregnancyregistry.org.

Risk Summary

Available data from published literature, including the Transplant Pregnancy Registry International, observational cohort studies, case-controlled studies, meta-analysis, case series, and case reports, over decades of use with cyclosporine in pregnancy have not identified a drug associated risk of major birth defects, or miscarriage. Adverse maternal or fetal outcomes including hypertension, preeclampsia, preterm birth, and low birth weight are increased in patients treated with cyclosporine. However, patients receiving cyclosporine during pregnancy have underlying medical conditions and may be treated with concomitant medications that limit the interpretability of these findings (see Data).

Embryo-fetal developmental (EFD) studies in rats and rabbits with cyclosporine have shown embryo-fetal toxicity at dose levels below the MRHD based on BSA.

The alcohol content of Sandimmune should be taken into account when given to pregnant women (see WARNINGS, Special Excipients).

The estimated background risk of major birth defects and miscarriage for the indicated populations is unknown. All pregnancies have a background risk of birth defect, loss, or other adverse outcomes. In the U.S. general population, the estimated background risk of major birth defects and miscarriage in clinically recognized pregnancies is 2% to 4% and 15% to 20%, respectively.

Data

Human Data

Available data from the National Transplantation Pregnancy Registry (NTPR) including 622 pregnancies in renal, liver, and heart transplant recipients exposed to cyclosporine during pregnancy found that the overall rate of major birth defects, live birth rates, and miscarriage rates were comparable to the general population. Maternal and fetal adverse outcomes, including the rate of hypertension, preeclampsia, premature births, and low birth weight infants appear to be increased in transplant recipients treated with cyclosporine compared to the general population. However, these patients have underlying medical conditions that confound the above findings.

Animal Data

Animal studies have shown reproductive toxicity in rats and rabbits.

Three EFD studies (two oral and one intravenous) are available in rats. In two EFD studies, pregnant rats were orally administered with cyclosporine either at doses of 10, 17, 30, 100 and 300 mg/kg/day or 4, 10 and 25 mg/kg/day from gestation day (GD) 6 to 15 or from GD 7 to 17, respectively. Maternal toxicity characterized by mortality, clinical signs of toxicity and impaired body weight gain were observed at 30 mg/kg/day and above. Cyclosporine was embryo- and fetotoxic as indicated by increased embryonic mortality and reduced fetal weight together with skeletal retardations in rats at 25 mg/kg/day and above. In addition, ventricular septal defect was observed at 25 mg/kg/day in fetuses. In the first study, the oral no observed effect level (NOEL) for both dams and fetuses was 17 mg/kg/day (0.2 times the MRHD based on BSA). In the other oral study, the NOEL for dams and fetuses were 10 and 4 mg/kg/day (0.13 and 0.05 times the MRHD based on BSA), respectively. In the IV EFD study, rats were administered with 3, 6 and 12 mg/kg/day of cyclosporine from GD 7 to 17. An increase in post implantation loss was observed at 12 mg/kg/day; ventricular septal defect was observed at ≥ 6 mg/kg/day in fetuses. The IV NOEL for dams and fetus were 6 and 3 mg/kg/day (below the MRHD based on BSA), respectively after IV administration.

In rabbits, cyclosporine was orally administered at dose levels of 10, 30, 100 or 300 mg/kg/day from GD 6 to 18. At 100 mg/kg/day and above, reduction in body weight gain of dams and at 300 mg/kg/day abortions were observed. Maternal toxicity, embryo-fetotoxicity as indicated by increased pre- and postnatal mortality, reduced fetal weight together with skeletal retardations were observed at 100 mg/kg/day and above. The NOEL for dams and fetuses was 30 mg/kg/day (1 times the MRHD based on BSA).

In two published research studies, rabbits exposed to cyclosporine in utero (10 mg/kg/day subcutaneously) demonstrated reduced numbers of nephrons, renal hypertrophy, systemic hypertension and progressive renal insufficiency up to 35 weeks of age. These findings have not been demonstrated in other species and their relevance for humans is unknown.

In a peri- and postnatal development study in rats, pregnant rats were orally administered with cyclosporine (5, 15 or 45 mg/kg/day) from GD 15 until end of lactation. At 45 mg/kg/day (0.5 times the MRHD based on BSA), increased pre and postnatal mortality of offspring and reduced body weight gain of surviving pups were observed. Cyclosporine up to 15 mg/kg/day (0.2 times the MRHD based on BSA) had no effect on pregnancy, pre and postnatal development of offspring.

Nursing Mothers

Cyclosporine and its metabolites are present in human milk following oral and intravenous administration. Adverse effects on the breastfed infant have not been reported. There are no data on the effects of the drug on milk production. The alcohol content of Sandimmune should be taken into account when given to lactating women (see WARNINGS, Special Excipients). Lactating women are encouraged to avoid additional alcohol intake during treatment. The developmental and health benefits of breastfeeding should be considered along with the mother's clinical need for Sandimmune and any potential adverse effects on the breastfed infant from Sandimmune or from the underlying maternal condition.

Pediatric Use

Although no adequate and well-controlled studies have been conducted in children, patients as young as 6 months of age have received the drug with no unusual adverse effects.

Geriatric Use

Clinical studies of Sandimmune (cyclosporine) did not include sufficient numbers of subjects aged 65 and over to determine whether they respond differently from younger patients. Other reported clinical experience has not identified differences in responses between the elderly and younger patients. In general, dose selection for an elderly patient should be cautious, usually starting at the low end of the dosing range, reflecting the greater frequency of decreased hepatic, renal, or cardiac function, and of concomitant disease or other drug therapy.

ADVERSE REACTIONS

The principal adverse reactions of Sandimmune (cyclosporine) therapy are renal dysfunction, tremor, hirsutism, hypertension, and gum hyperplasia.

Hypertension

Hypertension, which is usually mild to moderate, may occur in approximately 50% of patients following renal transplantation and in most cardiac transplant patients.

Glomerular Capillary Thrombosis

Glomerular capillary thrombosis has been found in patients treated with cyclosporine and may progress to graft failure. The pathologic changes resemble those seen in the hemolytic-uremic syndrome and include thrombosis of the renal microvasculature, with platelet-fibrin thrombi occluding glomerular capillaries and afferent arterioles, microangiopathic hemolytic anemia, thrombocytopenia, and decreased renal function. Similar findings have been observed when other immunosuppressives have been employed post transplantation.

Hypomagnesemia

Hypomagnesemia has been reported in some, but not all, patients exhibiting convulsions while on cyclosporine therapy. Although magnesium-depletion studies in normal subjects suggest that hypomagnesemia is associated with neurologic disorders, multiple factors, including hypertension, high-dose methylprednisolone, hypocholesterolemia, and nephrotoxicity associated with high plasma concentrations of cyclosporine appear to be related to the neurological manifestations of cyclosporine toxicity.

Clinical Studies

The following reactions occurred in 3% or greater of 892 patients involved in clinical trials of kidney, heart, and liver transplants:

 | Randomized Kidney Patients |  | All Sandimmune (cyclosporine) Patients
 | Sandimmune | Azathioprine | Kidney | Heart | Liver
Body System/ | (N = 227) | (N = 228) | (N = 705) | (N = 112) | (N = 75)
Adverse Reactions | % | % | % | % | %
Genitourinary
Renal Dysfunction | 32 | 6 | 25 | 38 | 37
Cardiovascular
Hypertension | 26 | 18 | 13 | 53 | 27
Cramps | 4 | < 1 | 2 | < 1 | 0
Skin
Hirsutism | 21 | < 1 | 21 | 28 | 45
Acne | 6 | 8 | 2 | 2 | 1
Central Nervous System
Tremor | 12 | 0 | 21 | 31 | 55
Convulsions | 3 | 1 | 1 | 4 | 5
Headache | 2 | < 1 | 2 | 15 | 4
Gastrointestinal
Gum Hyperplasia | 4 | 0 | 9 | 5 | 16
Diarrhea | 3 | < 1 | 3 | 4 | 8
Nausea/Vomiting | 2 | < 1 | 4 | 10 | 4
Hepatotoxicity | < 1 | < 1 | 4 | 7 | 4
Abdominal Discomfort | < 1 | 0 | < 1 | 7 | 0
Autonomic Nervous System
Paresthesia | 3 | 0 | 1 | 2 | 1
Flushing | < 1 | 0 | 4 | 0 | 4
Hematopoietic
Leukopenia | 2 | 19 | < 1 | 6 | 0
Lymphoma | < 1 | 0 | 1 | 6 | 1
Respiratory
Sinusitis | < 1 | 0 | 4 | 3 | 7
Miscellaneous
Gynecomastia | < 1 | 0 | < 1 | 4 | 3

The following reactions occurred in 2% or less of patients: allergic reactions, anemia, anorexia, confusion, conjunctivitis, edema, fever, brittle fingernails, gastritis, hearing loss, hiccups, hyperglycemia, muscle pain, peptic ulcer, thrombocytopenia, tinnitus.

The following reactions occurred rarely: anxiety, chest pain, constipation, depression, hair breaking, hematuria, joint pain, lethargy, mouth sores, myocardial infarction, night sweats, pancreatitis, pruritus, swallowing difficulty, tingling, upper GI bleeding, visual disturbance, weakness, weight loss.

Renal Transplant Patients in Whom Therapy Was Discontinued
 | Randomized Patients |  | All Sandimmune Patients
 | Sandimmune | Azathioprine
 | (N = 227) | (N = 228) | (N = 705)
Reason for Discontinuation | % | % | %
Renal Toxicity | 5.7 | 0 | 5.4
Infection | 0 | 0.4 | 0.9
Lack of Efficacy | 2.6 | 0.9 | 1.4
Acute Tubular Necrosis | 2.6 | 0 | 1.0
Lymphoma/Lymphoproliferative Disease | 0.4 | 0 | 0.3
Hypertension | 0 | 0 | 0.3
Hematological Abnormalities | 0 | 0.4 | 0
Other | 0 | 0 | 0.7
Sandimmune (cyclosporine) was discontinued on a temporary basis and then restarted in 18 additional patients.

Patients receiving immunosuppressive therapies, including cyclosporine and cyclosporine-containing regimens, are at increased risk of infections (viral, bacterial, fungal, and parasitic). Both generalized and localized infections can occur. Preexisting infections may also be aggravated. Fatal outcomes have been reported (see WARNINGS).

Infectious Complications in the Randomized Renal Transplant Patients
 | Sandimmune Treatment | Standard Treatment*
 | (N = 227) | (N = 228)
Complication | % of Complications | % of Complications
Septicemia | 5.3 | 4.8
Abscesses | 4.4 | 5.3
Systemic Fungal Infection | 2.2 | 3.9
Local Fungal Infection | 7.5 | 9.6
Cytomegalovirus | 4.8 | 12.3
Other Viral Infections | 15.9 | 18.4
Urinary Tract Infections | 21.1 | 20.2
Wound and Skin Infections | 7.0 | 10.1
Pneumonia | 6.2 | 9.2
*Some patients also received ALG.

Cremophor® EL (polyoxyethylated castor oil) is known to cause hyperlipemia and electrophoretic abnormalities of lipoproteins. These effects are reversible upon discontinuation of treatment but are usually not a reason to stop treatment.

Postmarketing Experience

Hepatotoxicity

Cases of hepatotoxicity and liver injury, including cholestasis, jaundice, hepatitis, and liver failure; serious and/or fatal outcomes have been reported (see WARNINGS, Hepatotoxicity).

Increased Risk of Infections

Cases of JC virus-associated progressive multifocal leukoencephalopathy (PML), sometimes fatal; and polyoma virus-associated nephropathy (PVAN), especially BK virus resulting in graft loss have been reported (see WARNINGS, Polyoma Virus Infection).

Headache, Including Migraine

Cases of migraine have been reported. In some cases, patients have been unable to continue cyclosporine, however, the final decision on treatment discontinuation should be made by the treating physician following the careful assessment of benefits versus risks.

Pain of Lower Extremities

Isolated cases of pain of lower extremities have been reported in association with cyclosporine. Pain of lower extremities has also been noted as part of Calcineurin-Inhibitor Induced Pain Syndrome (CIPS) as described in the literature.

OVERDOSAGE

There is a minimal experience with overdosage. Because of the slow absorption of Sandimmune Soft Gelatin Capsules or Oral Solution, forced emesis and gastric lavage would be of value up to 2 hours after administration. Transient hepatotoxicity and nephrotoxicity may occur which should resolve following drug withdrawal. Oral doses of cyclosporine up to 10 g (about 150 mg/kg) have been tolerated with relatively minor clinical consequences, such as vomiting, drowsiness, headache, tachycardia, and in a few patients, moderately severe, reversible impairment of renal function. However, serious symptoms of intoxication have been reported following accidental parenteral overdosage with cyclosporine in premature neonates. General supportive measures and symptomatic treatment should be followed in all cases of overdosage. Sandimmune (cyclosporine) is not dialyzable to any great extent, nor is it cleared well by charcoal hemoperfusion. The oral LD50 is 2329 mg/kg in mice, 1480 mg/kg in rats, and > 1000 mg/kg in rabbits. The intravenous (IV) LD50 is 148 mg/kg in mice, 104 mg/kg in rats, and 46 mg/kg in rabbits.

DOSAGE AND ADMINISTRATION

Sandimmune Soft Gelatin Capsules (cyclosporine capsules, USP) and Sandimmune Oral Solution (cyclosporine oral solution, USP) have decreased bioavailability in comparison to Neoral Soft Gelatin Capsules (cyclosporine capsules, USP) MODIFIED and Neoral Oral Solution (cyclosporine oral solution, USP) MODIFIED. Sandimmune and Neoral are not bioequivalent and cannot be used interchangeably without physician supervision.

The initial oral dose of Sandimmune (cyclosporine) should be given 4 to 12 hours prior to transplantation as a single dose of 15 mg/kg. Although a daily single dose of 14 to 18 mg/kg was used in most clinical trials, few centers continue to use the highest dose, most favoring the lower end of the scale. There is a trend towards use of even lower initial doses for renal transplantation in the ranges of 10 to 14 mg/kg/day. The initial single daily dose is continued postoperatively for 1 to 2 weeks and then tapered by 5% per week to a maintenance dose of 5 to 10 mg/kg/day. Some centers have successfully tapered the maintenance dose to as low as 3 mg/kg/day in selected renal transplant patients without an apparent rise in rejection rate.

See Blood Concentration Monitoring, below.

Specific Populations

Renal Impairment

Cyclosporine undergoes minimal renal elimination and its pharmacokinetics do not appear to be significantly altered in patients with end-stage renal disease who receive routine hemodialysis treatments (see CLINICAL PHARMACOLOGY). However, due to its nephrotoxic potential (see WARNINGS), careful monitoring of renal function is recommended; cyclosporine dosage should be reduced if indicated (see WARNINGS and PRECAUTIONS).

Hepatic Impairment

The clearance of cyclosporine may be significantly reduced in severe liver disease patients (see CLINICAL PHARMACOLOGY). Dose reduction may be necessary in patients with severe liver impairment to maintain blood concentrations within the recommended target range (see WARNINGS and PRECAUTIONS).

Pediatrics

In pediatric usage, the same dose and dosing regimen may be used as in adults although in several studies, children have required and tolerated higher doses than those used in adults.

Adjunct therapy with adrenal corticosteroids is recommended. Different tapering dosage schedules of prednisone appear to achieve similar results. A dosage schedule based on the patient’s weight started with 2.0 mg/kg/day for the first 4 days tapered to 1.0 mg/kg/day by 1 week, 0.6 mg/kg/day by 2 weeks, 0.3 mg/kg/day by 1 month, and 0.15 mg/kg/day by 2 months and thereafter as a maintenance dose. Another center started with an initial dose of 200 mg tapered by 40 mg/day until reaching 20 mg/day. After 2 months at this dose, a further reduction to 10 mg/day was made. Adjustments in dosage of prednisone must be made according to the clinical situation.

To make Sandimmune Oral Solution (cyclosporine oral solution, USP) more palatable, the oral solution may be diluted with milk, chocolate milk, or orange juice preferably at room temperature. Patients should avoid switching diluents frequently. Sandimmune Soft Gelatin Capsules and Oral Solution should be administered on a consistent schedule with regard to time of day and relation to meals.

Take the prescribed amount of Sandimmune (cyclosporine) from the container using the dosage syringe supplied after removal of the protective cover, and transfer the solution to a glass of milk, chocolate milk, or orange juice. Stir well and drink at once. Do not allow to stand before drinking. It is best to use a glass container and rinse it with more diluent to ensure that the total dose is taken. After use, replace the dosage syringe in the protective cover. Do not rinse the dosage syringe with water or other cleaning agents either before or after use. If the dosage syringe requires cleaning, it must be completely dry before resuming use. Introduction of water into the product by any means will cause variation in dose.

Sandimmune® Injection (cyclosporine injection, USP)

FOR INFUSION ONLY

Note: Anaphylactic reactions have occurred with Sandimmune Injection (cyclosporine injection, USP). See WARNINGS.

Patients unable to take Sandimmune Soft Gelatin Capsules or Oral Solution pre- or postoperatively may be treated with the intravenous (IV) concentrate. Sandimmune Injection (cyclosporine injection, USP) is administered at 1/3 the oral dose. The initial dose of Sandimmune Injection (cyclosporine injection, USP) should be given 4 to 12 hours prior to transplantation as a single intravenous dose of 5 to 6 mg/kg/day. This daily single dose is continued postoperatively until the patient can tolerate the soft gelatin capsules or oral solution. Patients should be switched to Sandimmune Soft Gelatin Capsules or Oral Solution as soon as possible after surgery. In pediatric usage, the same dose and dosing regimen may be used, although higher doses may be required.

Adjunct steroid therapy is to be used (See aforementioned).

Immediately before use, the intravenous concentrate should be diluted 1 mL Sandimmune Injection (cyclosporine injection, USP) in 20 mL to 100 mL 0.9% Sodium Chloride Injection or 5% Dextrose Injection using appropriate aseptic technique and given in a slow intravenous infusion over 2 to 6 hours.

Based on the chemical and physical in-use stability data, the infusion should be completed within 6 hours at room temperature. Discard any unused diluted solution. If not administered immediately, the diluted solution can be stored at 2°C to 8°C (under refrigeration), provided that the total duration for both storage and infusion is less than 24 hours.

The Cremophor® EL (polyoxyethylated castor oil) contained in the concentrate for intravenous infusion can cause phthalate stripping from PVC.

Parenteral drug products should be inspected visually for particulate matter and discoloration prior to administration, whenever solution and container permit.

Blood Concentration Monitoring

Several study centers have found blood concentration monitoring of cyclosporine useful in patient management. While no fixed relationships have yet been established, in one series of 375 consecutive cadaveric renal transplant recipients, dosage was adjusted to achieve specific whole blood 24-hour trough concentrations of 100 to 200 ng/mL as determined by high-pressure liquid chromatography (HPLC).

Of major importance to blood concentration analysis is the type of assay used. The above concentrations are specific to the parent cyclosporine molecule and correlate directly to the new monoclonal specific radioimmunoassays (mRIA-sp). Nonspecific assays are also available which detect the parent compound molecule and various of its metabolites. Older studies often cited concentrations using a nonspecific assay which were roughly twice those of specific assays. Assay results are not interchangeable and their use should be guided by their approved labeling. If plasma specimens are employed, concentrations will vary with the temperature at the time of separation from whole blood. Plasma concentrations may range from 1/2 to 1/5 of whole blood concentrations. Refer to individual assay labeling for complete instructions. In addition, Transplantation Proceedings (June 1990) contains position papers and a broad consensus generated at the Cyclosporine-Therapeutic Drug Monitoring conference that year. Blood concentration monitoring is not a replacement for renal function monitoring or tissue biopsies.

HOW SUPPLIED

Sandimmune® Soft Gelatin Capsules (cyclosporine capsules, USP)

25 mg: Oval, pink, branded “ 78/240”. Unit dose packages of 30 capsules,

3 blister cards of 10 capsules………………………………………………………….NDC 0078-0240-15

100 mg: Oblong, dusty rose, branded “ 78/241”. Unit dose packages of 30 capsules,

3 blister cards of 10 capsules………………………………………………………….NDC 0078-0241-15

Store and Dispense: Store at 20°C to 25°C (68°F to 77°F); excursions permitted between 15°C and 30°C (59°F and 86°F) [see USP Controlled Room Temperature].

An odor may be detected upon opening the unit dose container, which will dissipate shortly thereafter. This odor does not affect the quality of the product.

Sandimmune® Oral Solution (cyclosporine oral solution, USP)

Supplied in 50 mL bottles containing 100 mg of cyclosporine per mL NDC 0078-0110-22

A dosage syringe is provided for dispensing.

Store and Dispense: In the original container at temperatures below 30°C (86°F). Do not store in the refrigerator. Protect from freezing. Once opened, the contents must be used within 2 months.

Sandimmune® Injection (cyclosporine injection, USP)

FOR INTRAVENOUS INFUSION

Supplied as a 5 mL sterile ampul containing 50 mg of cyclosporine per mL,

in boxes of 10 ampuls…………………………………………………………………..NDC 0078-0109-01

Store and Dispense: At temperatures below 30°C (86°F). Protect from light.

FOR INFUSION ONLY

*Cremophor® is the registered trademark of BASF Aktiengesellschaft.

Distributed by:

Novartis Pharmaceuticals Corporation
East Hanover, New Jersey 07936

© Novartis

Revised: May 2025

T2025-29

PRINCIPAL DISPLAY PANEL

NDC 0078-0240-15

25 mg

30 SOFT GELATIN CAPSULES

SANDIMMUNE® Soft Gelatin Capsules

(cyclosporine capsules, USP)

Each 25 mg capsule contains:

cyclosporine, USP 25 mg

alcohol, USP dehydrated max 12.7% by volume

Inactive Ingredients: corn oil, gelatin, iron oxide red, linoleoyl macrogolglycerides, sorbitol, and titanium dioxide. May also contain glycerol.

WARNING: Sandimmune® (cyclosporine capsules, USP) is

NOT BIOEQUIVALENT to Neoral® (cyclosporine capsules, USP) MODIFIED.

Do NOT use interchangeably without a physician’s supervision.

Dosage:

See package insert for dosage information.

Rx only

NOVARTIS

PRINCIPAL DISPLAY PANEL

NDC 0078-0241-15

100 mg

30 SOFT GELATIN CAPSULES

SANDIMMUNE® Soft Gelatin Capsules

(cyclosporine capsules, USP)

Each 100 mg capsule contains:

cyclosporine, USP 100 mg

alcohol, USP dehydrated max 12.7% by volume

Inactive Ingredients: corn oil, gelatin, iron oxide red, linoleoyl macrogolglycerides, sorbitol, and titanium dioxide. May also contain glycerol or iron oxide yellow.

WARNING: Sandimmune® (cyclosporine capsules, USP) is

NOT BIOEQUIVALENT to Neoral® (cyclosporine capsules, USP) MODIFIED.

Do NOT use interchangeably without a physician’s supervision.

Dosage:

See package insert for dosage information.

Rx only

NOVARTIS

PRINCIPAL DISPLAY PANEL

NDC 0078-0110-22

50 mL

SANDIMMUNE® Oral Solution

(cyclosporine oral solution, USP)

100 mg/mL

WARNING: Sandimmune® (cyclosporine
oral solution, USP) is NOT BIOEQUIVALENT
to Neoral® (cyclosporine oral solution, USP)
MODIFIED. Do NOT use interchangeably
without a physician’s supervision.

Each mL contains:

cyclosporine, USP 100 mg

dehydrated alcohol, Ph. Helv 12.5%

Rx only

NOVARTIS

PRINCIPAL DISPLAY PANEL

NDC 0078-0109-01

Sandimmune® Injection

(cyclosporine injection, USP)

Sterile solution for intravenous infusion only

Rx only

FOR INFUSION ONLY. DILUTE BEFORE USE.

250 mg (5 mL ampul)
10 Ampuls

NOVARTIS